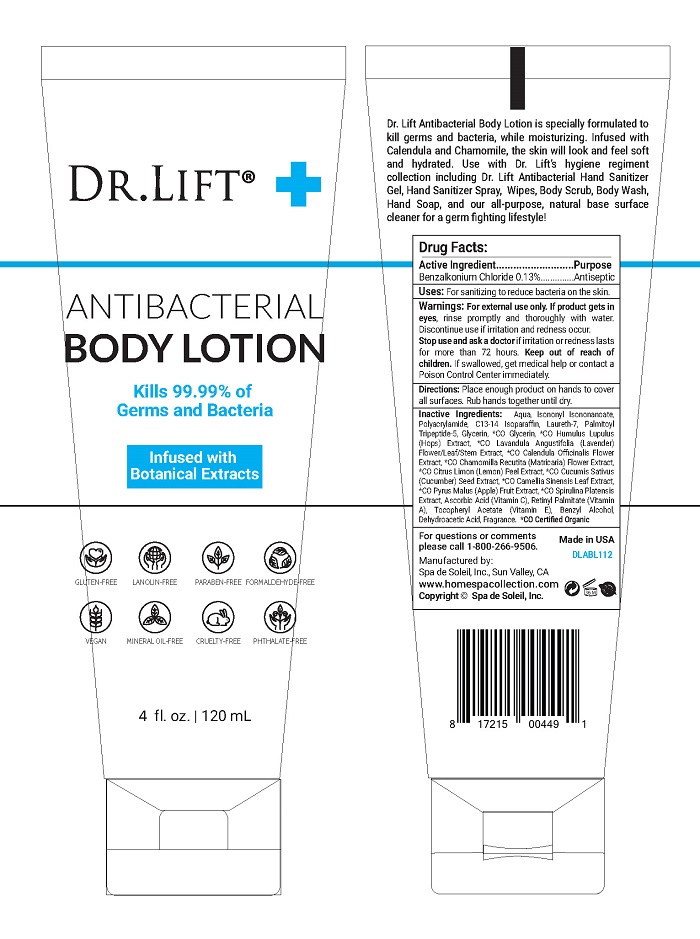 DRUG LABEL: Dr Lift Antibacterial
NDC: 68062-2243 | Form: LOTION
Manufacturer: Spa de Soleil
Category: otc | Type: HUMAN OTC DRUG LABEL
Date: 20251010

ACTIVE INGREDIENTS: BENZALKONIUM CHLORIDE 0.156 mg/120 mg
INACTIVE INGREDIENTS: GLYCERIN; WATER

Dr Lift Antibacterial Body Lotion

Active Ingredient

Benzalkonium Chloride 0.13%

Purpose

Antiseptic

Warnings

For external use only. If product gets in eyes, rinse promptly and thoroughly with water. Discontinue use if irritation and redness occur.

Stop use and ask a doctor if irritation or redness lasts for more than 72 hours. Keep out of reach of children. If swallowed, get medical help or contact a Poison Control Center immediately.

Keep out of reach of children.

Directions

Place enough product in the palm of your hands to thoroughly cover your hands. Rub hands together until dry.

DOSAGE AND ADMINISTRATION

Place enough product in the palm of your hands to thoroughly cover you hands. Rub hands together briskly until product is completely absorbed and hands are dry.

Inactive Ingredients:

Inactive Ingredients

Aqua, Isononyl Isononanoate, Polyacrylamide, C13-14 Isoparaffin, Laureth-7, Palmitoyl Tripeptide-5, Glycerin, *CO Glycerin, *CO Humulus Lupulus (Hops) Extract, *CO Lavandula Angustifolia (Lavender) Flower/Leaf/Stem Extract, *CO Calendula Officinalis Flower Extract, *CO Chamomilla Recutita (Matricaria) Flower Extract, *CO Citrus Limon (Lemon) Peel Extract, *CO Cucumis Sativus (Cucumber) Seed Extract, *CO Camellia Sinensis Leaf Extract, *CO Pyrus Malus (Apple) Fruit Extract, *CO Spirulina Platensis Extract, Ascorbic Acid (Vitamin C), Retinyl Palmitate (Vitamin A), Tocopheryl Acetate (Vitamin E), Benzyl Alcohol, Dehydroacetic Acid, Fragrance. *CO Certified Organic